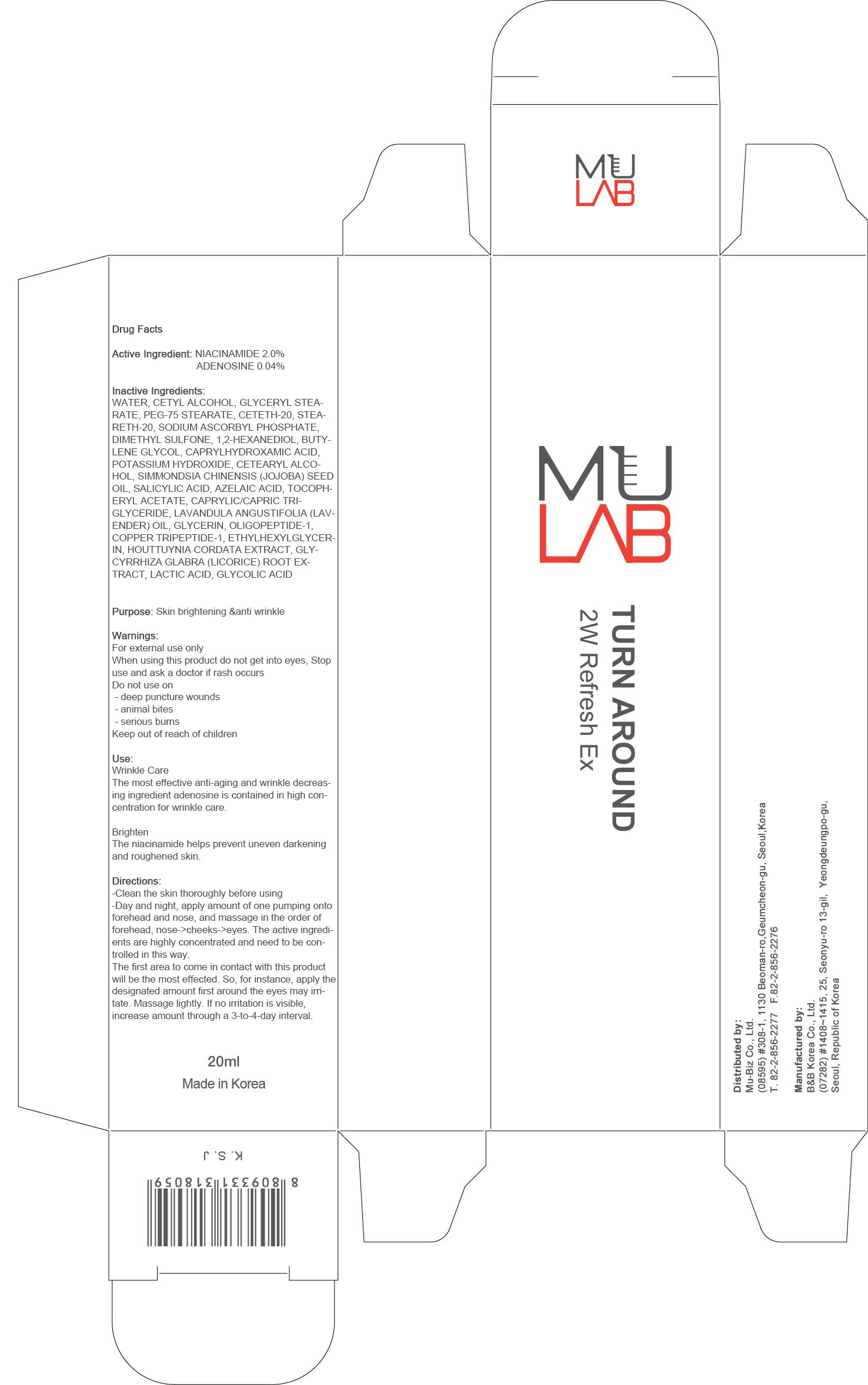 DRUG LABEL: MU LAB TURN AROUND 2W Refresh Ex
NDC: 71164-020 | Form: CREAM
Manufacturer: MU-Biz.co,.Ltd
Category: otc | Type: HUMAN OTC DRUG LABEL
Date: 20161230

ACTIVE INGREDIENTS: NIACINAMIDE 0.40 g/20 mL; ADENOSINE 0.008 g/20 mL
INACTIVE INGREDIENTS: WATER; CETYL ALCOHOL

ACTIVE INGREDIENT

Active Ingredient: NIACINAMIDE 2.0%, ADENOSINE 0.04%

INACTIVE INGREDIENT

Inactive Ingredients: WATER, CETYL ALCOHOL, GLYCERYL STEARATE, PEG-75 STEARATE, CETETH-20, STEARETH-20, SODIUM ASCORBYL PHOSPHATE, DIMETHYL SULFONE, 1,2-HEXANEDIOL, BUTYLENE GLYCOL, CAPRYLHYDROXAMIC ACID, POTASSIUM HYDROXIDE, CETEARYL ALCOHOL, SIMMONDSIA CHINENSIS (JOJOBA) SEED OIL, SALICYLIC ACID, AZELAIC ACID, TOCOPHERYL ACETATE, CAPRYLIC/CAPRIC TRIGLYCERIDE, LAVANDULA ANGUSTIFOLIA (LAVENDER) OIL, GLYCERIN, OLIGOPEPTIDE-1, COPPER TRIPEPTIDE-1, ETHYLHEXYLGLYCERIN, HOUTTUYNIA CORDATA EXTRACT, GLYCYRRHIZA GLABRA (LICORICE) ROOT EXTRACT, LACTIC ACID, GLYCOLIC ACID

PURPOSE

Purpose: Skin brightening & anti wrinkle

WARNINGS

Warnings: For external use only. When using this product do not get into eyes, Stop use and ask a doctor if rash occurs. Do not use on - deep puncture wounds - animal bites - serious burns. Keep out of reach of children.

KEEP OUT OF REACH OF CHILDREN

Use

Wrinkle Care- The most effective anti-aging and wrinkle decreasing ingredient adenosine is contained in high concentration for wrinkle care.

Brighten- The niacinamide helps prevent uneven darkening and roughened skin.

Directions

Directions: - Clean the skin thoroughly before using - Day and night, apply amount of one pumping onto forehead and nose, and massage in the order of forehead, nose->cheeks->eyes. The active ingredients are highly concentrated and need to be controlled in this way. The first area to come in contact with this product will be the most effected. So, for instance, apply the designated amount first around the eyes may irritate. Massage lightly. If no irritation is visible, increase amount through a 3-to-4-day interval.